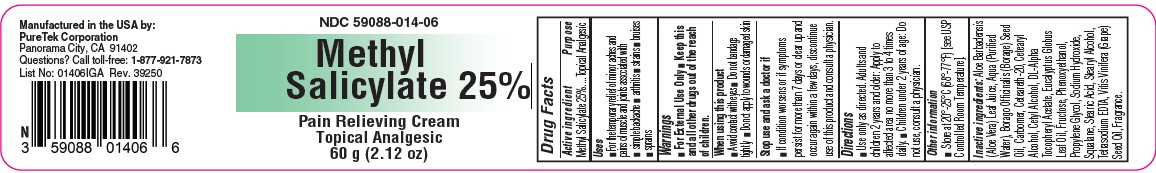 DRUG LABEL: Methyl Salicylate 25%
NDC: 59088-014 | Form: CREAM
Manufacturer: Puretek Corporation
Category: otc | Type: HUMAN OTC DRUG LABEL
Date: 20250715

ACTIVE INGREDIENTS: METHYL SALICYLATE 250 mg/1 g
INACTIVE INGREDIENTS: PROPYLENE GLYCOL; .ALPHA.-TOCOPHEROL ACETATE; STEARIC ACID; CETEARETH-20; AQUA; PHENOXYETHANOL; FRUCTOSE; CETEARYL ALCOHOL; VITIS VINIFERA (GRAPE) SEED OIL; CARBOMER; CETYL ALCOHOL; TETRASODIUM EDTA; EUCALYPTUS GLOBULUS LEAF OIL; ALOE VERA LEAF; SQUALANE; BORAGO OFFICINALIS SEED OIL; STEARYL ALCOHOL

NDC 59088-014 Methyl Salicylate 25%

Active Ingredients:

Methyl Salicylate 25%

Purpose:

Topical Analgesic

Uses:

■ For the temporary relief of minor aches and pains of muscle and joints associated with ■ simple backache ■ arthritis ■ strains ■ bruises ■ sprains

Warnings:

■ For External Use Only

KEEP OUT OF REACH OF CHILDREN

■ Keep this and all other drugs out of the reach of children.

When using this product

■ Avoid contact with eyes ■ Do not bandage tightly ■ Do not apply to wounds or broken skin

Stop use and ask doctor if

■ If condition worsens or if symptoms persist for more than 7 days or clear up and occur again within a few days, discontinue use of this product and consult a physician.

Directions

■ Use only as directed. Adults and children 2 years and older: Apply to affected area no more than 3 to 4 times daily. ■ Children under 2 years of age: Do not use, consult a physician.

Other information

■ Store at 20°-25°C (68°-77°F) [see USP Controlled Room Temperature].

Inactive ingredients:

Aloe Barbadensis (Aloe Vera) Leaf Juice, Aqua (Purified Water), Borago Officinalis (Borage) Seed Oil, Carbomer, Ceteareth-20, Cetearyl Alcohol, Cetyl Alcohol, DL-Alpha Tocopheryl Acetate, Eucalyptus Globus Leaf Oil, Fructose, Phenoxyethanol, Propylene Glycol, Sodium Hydroxide, Squalane, Stearic Acid, Stearyl Alcohol, Tetrasodium EDTA, Vitis Vinifera (Grape) Seed Oil, Fragrance.

Methyl Salicylate 25%

Manufactured by:
PureTek Corporation
Panorama City, CA 91402
For questions or information
call toll-free: 877-921-7873